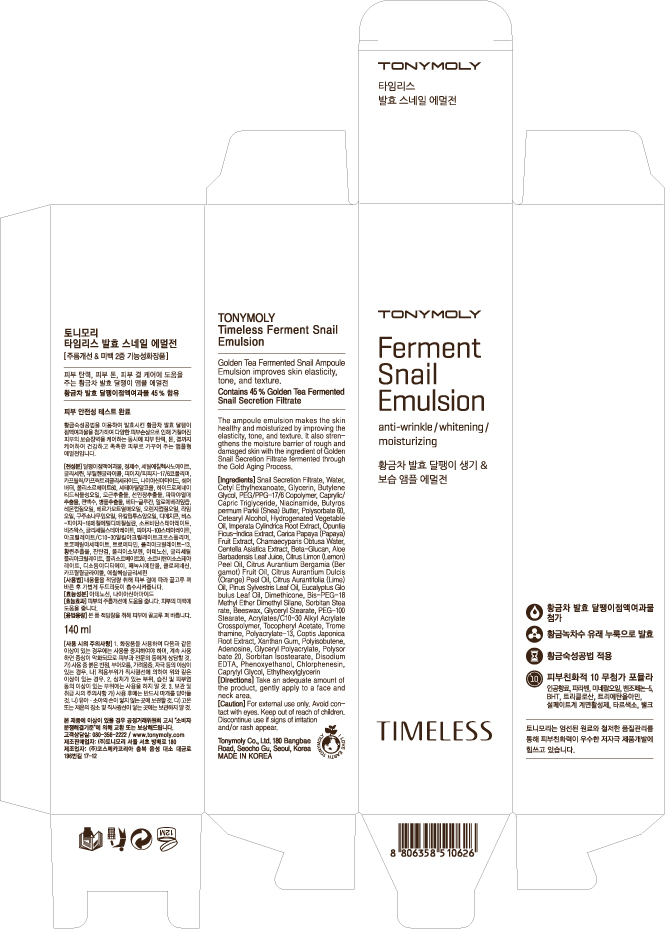 DRUG LABEL: TONYMOLY Timeless Ferment Snail Emulsion
NDC: 59078-101 | Form: EMULSION
Manufacturer: Tonymoly Co., Ltd.
Category: otc | Type: HUMAN OTC DRUG LABEL
Date: 20160202

ACTIVE INGREDIENTS: GLYCERIN 9694.3 mg/140 mL
INACTIVE INGREDIENTS: CETYL ETHYLHEXANOATE; POLYSORBATE 60; BIS-PEG-18 METHYL ETHER DIMETHYL SILANE; SODIUM BENZOATE; PEG-100 STEARATE; DIMETHICONE; TROMETHAMINE; PHENOXYETHANOL; CHLORPHENESIN; ETHYLHEXYLGLYCERIN; XANTHAN GUM; ADENOSINE; SORBITAN ISOSTEARATE; POLYSORBATE 20; POTASSIUM SORBATE; BUTYLENE GLYCOL; WATER; PEG/PPG-17/6 COPOLYMER; NIACINAMIDE; CAPRYLYL GLYCOL; MEDIUM-CHAIN TRIGLYCERIDES; SHEA BUTTER; CETOSTEARYL ALCOHOL; GLYCERYL MONOSTEARATE; SORBITAN MONOSTEARATE; YELLOW WAX; CHAMAECYPARIS OBTUSA WHOLE; LEMON OIL; IMPERATA CYLINDRICA ROOT; BERGAMOT OIL; EDETATE DISODIUM; OPUNTIA FICUS-INDICA; COPTIS JAPONICA ROOT; ORANGE OIL; LIME OIL; POLYETHYLENE GLYCOL 400; PINE NEEDLE OIL (PINUS SYLVESTRIS); EUCALYPTUS GLOBULUS LEAF; CENTELLA ASIATICA; ALOE VERA LEAF; PAPAYA; CITRIC ACID MONOHYDRATE

Active Ingredients

Glycerin 5.50%

Purpose

Wrinkle, Whitening

Use

Golden Tea Fermented Snail Ampoule Emulsion improves skin elasticity, tone, and texture.

Contains 45% Golden Tea Fermented Snail Secretion Filtrate

The ampoule emulsion makes the skin healthy and moisturized by improving the elasticity, tone, and texture. It also strengthens the moisture barrier of rough and damaged skin with the ingredient of Golden Snail Secretion Filtrate fermented through the Gold Aging Process.

Dosage

Take an adequate amount of the product, gently apply to a face and neck area.

Caution

For external use only. Avoid contact with eyes. Keep out of reach of children. Discontinue use if signs of imitation and/or rash appear.

Keep out of reach of children. Discontinue use if signs of imitation and/or rash appear.

Directions

Take an adequate amount of the product, gently apply to a face and neck area.

Inactive Ingredients

Snail Secretion Filtrate, Butylene Glycol, Water, Cetyl Ethylhexanoate, PEG/PPG-17/6 Copolymer, Caprylic/Capric Triglyceride, Niacinamide, Butyrospermum Parkii (Shea) Butter, Polysorbate 60, Cetearyl Alcohol, Hydrogenated Vegetable Oil, Bis-PEG-18 Methyl Ether Dimethyl Silane, Glyceryl Stearate, PEG-100 Stearate, Sorbitan Stearate, Dimethicone, Acrylates/C10-30 Alkyl Acrylate Crosspolymer, Beeswax, Polyacrylate-13, Tromethamine, Phenoxyethanol, Chlorphenesin, Tocopheryl Acetate, Polyisobutene, Ethylhexylglycerin, Caprylyl Glycol, Xanthan Gum, Chamaecyparis Obtusa Water, Citrus Medica Limonum (Lemon) Peel Oil, Adenosine, Imperata Cylindrica Root Extract, Glyceryl Polyacrylate, Sorbitan Isostearate, Polysorbate 20, Citrus Aurantium Bergamia (Bergamot) Fruit Oil, Disodium EDTA, Opuntia Ficus-Indica Extract, Coptis Japonica Root Extract, Propanediol, Citrus aurantium dulcis (orange) peel oil, Citrus Aurantifolia (Lime) Oil, PEG-8, Pinus Sylvestris Leaf Oil, Eucalyptus Globulus Leaf Oil, Centella Asiatica Extract, Carbomer, Aloe Barbadensis Leaf Juice, Carica papaya (papaya) fruit Extract, Beta-Glucan, Potassium sorbate, Sodium Benzoate, Citric Acid